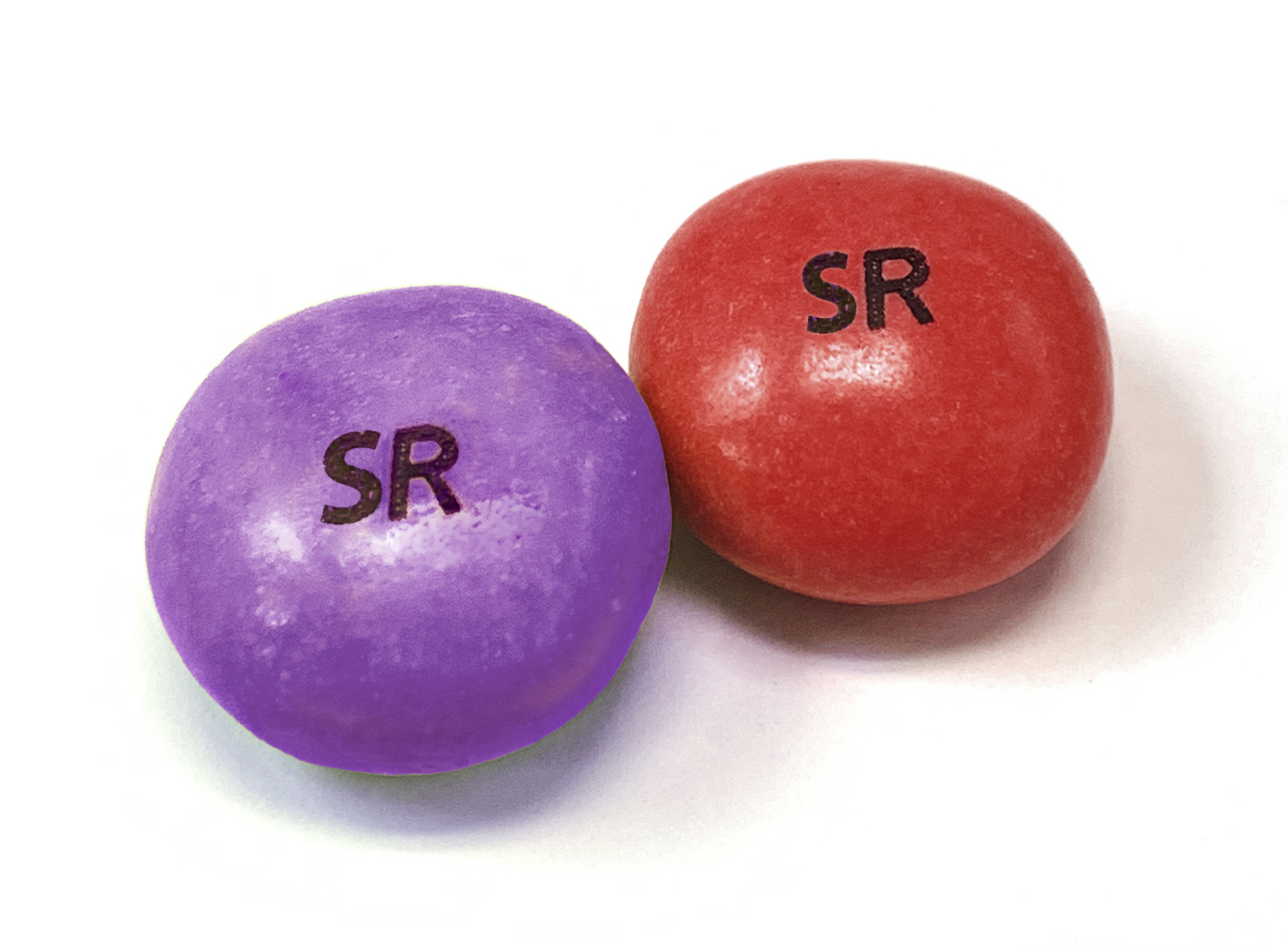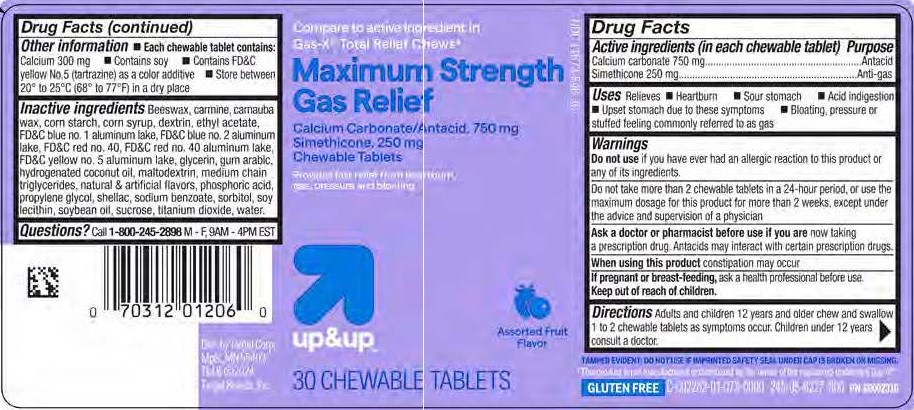 DRUG LABEL: Target Gas Relief Chews Mixed Berry and Strawberry
NDC: 11673-548 | Form: TABLET, CHEWABLE
Manufacturer: Target
Category: otc | Type: HUMAN OTC DRUG LABEL
Date: 20251220

ACTIVE INGREDIENTS: DIMETHICONE 250 mg/1 1; CALCIUM CARBONATE 750 mg/1 1
INACTIVE INGREDIENTS: WATER

Calcium carbonate 750 mg
Simethicone 250 mg

Active ingredients (in each chewable tablet)

Calcium carbonate 750 mg

Simethicone 250 mg

Purpose

Antacid

Anti-gas

INDICATIONS AND USAGE

Uses Relieves

- Heartburn
- Sour stomach
- Acid indigestion
- Upset stomach due to these symptoms
- Bloating, pressure or stuffed feeling commonly referred to as gas

Warnings

Do not use if you have ever had an allergic reaction to this product or any of its ingredients.

Do not take more than 2 chewable tablets in a 24-hour period, or use the maximum dosage for this product for more than 2 weeks, except under the advice and supervision of a physician

Ask a doctor or pharmacist before use if you are now taking a prescription drug. Antacids may interact with certain prescription drugs.

When using this product constipation may occur

PREGNANCY OR BREAST FEEDING

If pregnant or breast-feeding, ask a health professional before use.

Keep out of reach of children.

Directions

Adults and children 12 years and older chew and swallow 1 to 2 chewable tablets as symptoms occur. Children under 12 years consult a doctor.

Other information

- Each chewable tablet contains: Calcium 300 mg
- Contains soy
- Store between 20° and 25°C (68° to 77°F) in a dry place

INACTIVE INGREDIENT

Inactive ingredients: Beeswax, carmine, carnauba wax, corn starch, corn syrup, dextrin, ethyl acetate, FD&C blue no. 1 aluminum lake, FD&C blue no. 2 aluminum lake, FD&C red no. 40, FD&C red no. 40 aluminum lake, FD&C yellow no. 5 aluminum lake, glycerin, gum arabic, hydrogenated coconut oil, maltodextrin, medium chain triglycerides, natural & artificial flavors, phosphoric acid, propylene glycol, shellac, sodium benzoate, sorbitol, soy lecithin, soybean oil, sucrose, titanium dioxide, water.

QUESTIONS

Questions? Call 1-800-245-2898 Monday - Friday, 9AM - 4PM EST